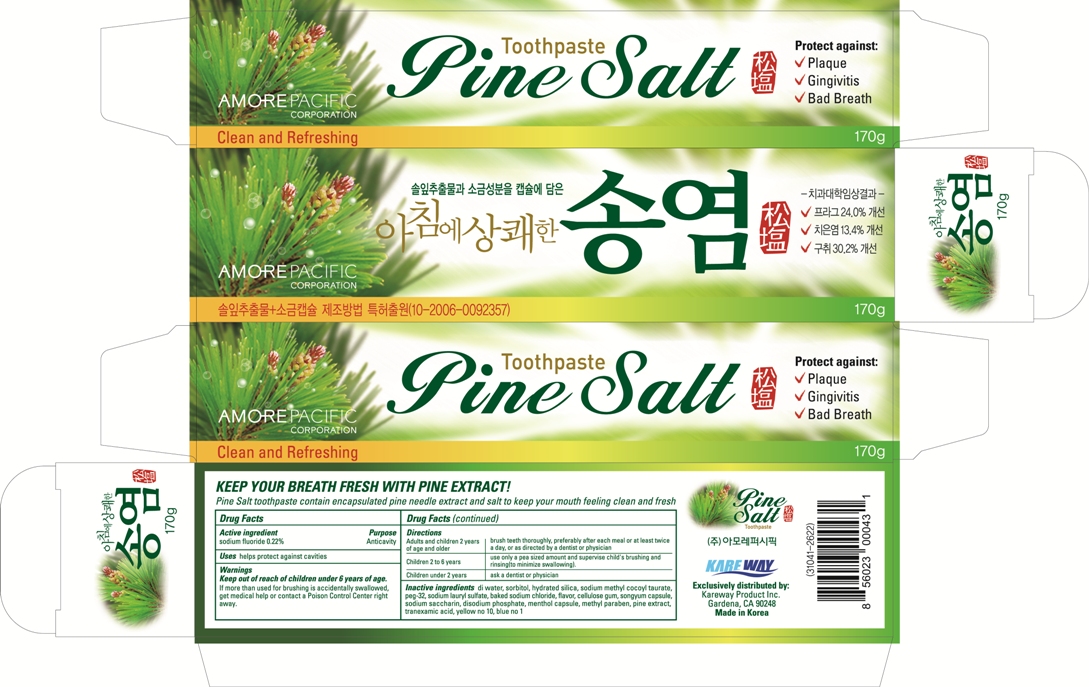 DRUG LABEL: Pine Salt
NDC: 67510-0043 | Form: PASTE, DENTIFRICE
Manufacturer: Kareway Product, Inc.
Category: otc | Type: HUMAN OTC DRUG LABEL
Date: 20110819

ACTIVE INGREDIENTS: SODIUM FLUORIDE 2.2 mg/1 g
INACTIVE INGREDIENTS: WATER; SORBITOL; HYDRATED SILICA; SODIUM METHYL COCOYL TAURATE; PEG-32 STEARATE; SODIUM LAURYL SULFATE; SODIUM CHLORIDE; CROSCARMELLOSE SODIUM; SACCHARIN SODIUM; SODIUM PHOSPHATE, DIBASIC; MENTHOL; METHYLPARABEN; PINUS STROBUS BARK

Drug Facts

Active ingredient

sodium fluoride 0.22%

Purpose

Anticavity

Uses

helps protect against cavities

Warnings

Enter section text here

Keep out of reach of children under 6 years of age.

If more than used for brushing is accidentally swallowed, get medical help or contact a Poison Control Center right away.

Directions

Adults and children 2 years of age and older | brush teeth thoroughly, preferably after each meal or at least twice a day, or as directed by a dentist or physician
Children 2 to 6 years | use only a pea sized amount and supervise child's brushing and rinsing (to minimize swallowing).
Children under 2 years | ask a dentist or physician

Inactive ingredients

di water, sorbitol, hydrated silica, sodium methyl cocoyl taurate, peg-32, sodium lauryl sulfate, baked sodium chloride, flavor, cellulose gum, songyum capsule, sodium saccharin, disodium phosphate, menthol capsule, methyl paraben, pine extract, tranexamic acid, yellow no.10, blue no.1

Package label

Pine Salt Toothpaste